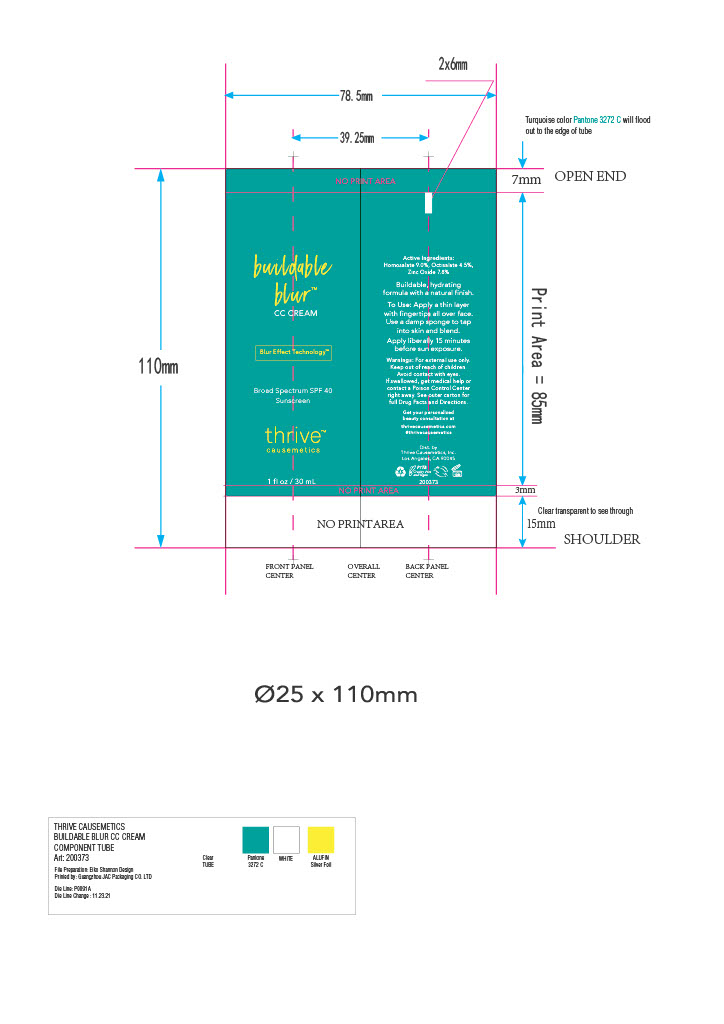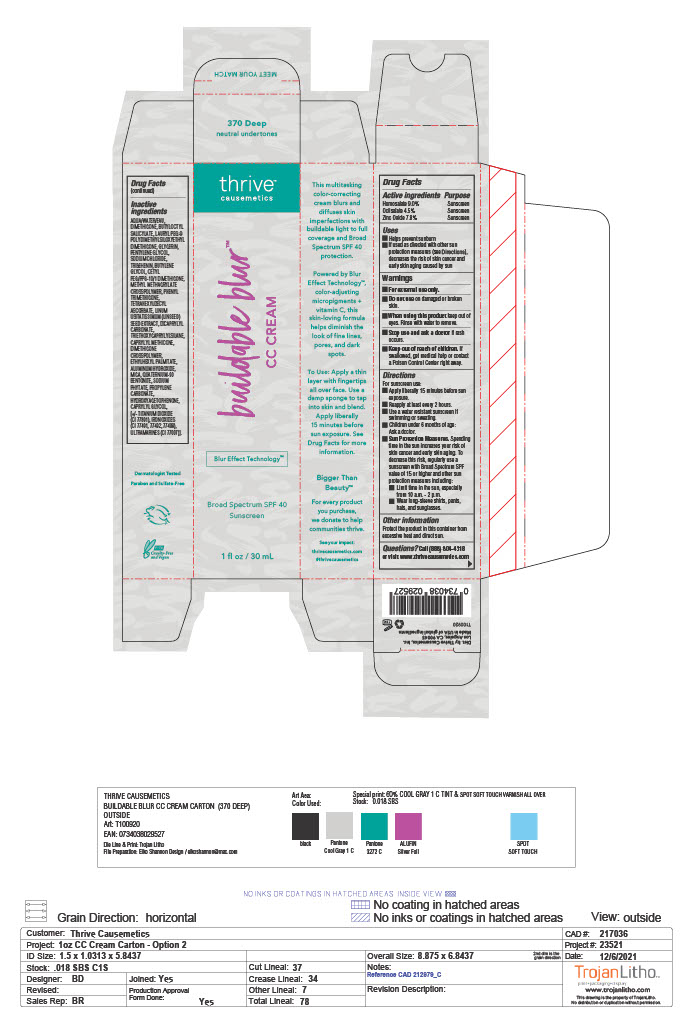 DRUG LABEL: Buildable Blur
NDC: 68577-148 | Form: CREAM
Manufacturer: COSMAX USA, CORPORATION
Category: otc | Type: HUMAN OTC DRUG LABEL
Date: 20241226

ACTIVE INGREDIENTS: HOMOSALATE 9 mg/100 mg; ZINC OXIDE 7.8 mg/100 mg; OCTISALATE 4.5 mg/100 mg
INACTIVE INGREDIENTS: WATER; SODIUM CHLORIDE; TETRAHEXYLDECYL ASCORBATE; DICAPRYLYL CARBONATE; ETHYLHEXYL PALMITATE; ALUMINUM HYDROXIDE; PHENYL TRIMETHICONE; FLAX SEED; TRIETHOXYCAPRYLYLSILANE; MICA; QUATERNIUM-90 BENTONITE; HYDROXYACETOPHENONE; DIMETHICONE; TRIBEHENIN; BUTYLENE GLYCOL; CETYL PEG/PPG-10/1 DIMETHICONE (HLB 1.5); PHYTATE SODIUM; BUTYLOCTYL SALICYLATE; PENTYLENE GLYCOL; CAPRYLYL TRISILOXANE; DIMETHICONE CROSSPOLYMER (450000 MPA.S AT 12% IN CYCLOPENTASILOXANE); PROPYLENE CARBONATE; TITANIUM DIOXIDE; FERRIC OXIDE RED; ULTRAMARINE BLUE; LAURYL PEG-9 POLYDIMETHYLSILOXYETHYL DIMETHICONE; GLYCERIN; METHYL METHACRYLATE/GLYCOL DIMETHACRYLATE CROSSPOLYMER; CAPRYLYL GLYCOL; FERRIC OXIDE YELLOW; FERROSOFERRIC OXIDE

THRIVE- Buildable Blur CC Cream SPF 40- 370 Deep (neutral undertones)

Active Ingredients

Homosalate 9.0%

Octisalate 4.5%

Zinc Oxide 7.8%

Purpose

Sunscreen

USES

- Helps prevent sunburn
- If used as directed with other sun protection measures (see Directions), decreases the risk of skin cancer and early skin aging caused by sun

Warnings

For external use only.

Do not useon damaged or broken skin

WHEN USING

When using this productkeep out of eyes. Rinse with water to remove.

Stop use and ask a doctorif rash occurs

Keep out of reach of children.If swallowed, get medical help or contact a Poison Control Center right away.

DIRECTIONS

For sunscreen use:

- Apply liberally 15 minutes before sun exposure
- Reapply at least every 2 hours
- Use a water resistant sunscreen if swimming or sweating
- Children under 6 months of age: Ask a doctor
  - Sun Protection Measures.Spending time in the sun increases your risk of skin cancer and early skin aging. To decrease the risk, regularly use a sunscreen with Broad Spectrum SPF value of 15 or higher and other sun protection measures including:

-Limit time in the sun, especially from 10 a.m. - 2 p.m.

-Wear long-sleeve shirts, pants, hats, and sunglasses.

OTHER INFORMATION

Protect the product in this container from excessive heat and direct sun

QUESTIONS

Questions? Call (888) 804-4318 or visit www.thrivecausemetics.com

Inactive ingredients

AQUA/WATER/EAU, DIMETHICONE, BUTYLOCTYL SALICYLATE, LAURYL PEG-9 POLYDIMETHYLSILOXYETHYL DIMETHICONE, GLYCERIN, PENTYLENE GLYCOL, SODIUM CHLORIDE, TRIBEHENIN, BUTYLENE GLYCOL, CETYL PEG/PPG-10/1 DIMETHICONE, METHYL METHACRYLATE CROSSPOLYMER, PHENYL TRIMETHICONE, TETRAHEXYLDECYL ASCORBATE, LINUM USITATISSIMUM (LINSEED) SEED EXTRACT, DICAPRYLYL CARBONATE, TRIETHOXYCAPRYLYLSILANE, CAPRYLYL METHICONE, DIMETHICONE CROSSPOLYMER, ETHYLHEXYL PALMITATE, ALUMINUM HYDROXIDE, MICA, QUATERNIUM-90 BENTONITE, SODIUM PHYTATE, PROPYLENE CARBONATE, HYDROXYACETOPHENONE, CAPRYLYL GLYCOL, [+/- TITANIUM DIOXIDE (CI 77891), IRON OXIDES (CI 77491, 77492, 77499), ULTRAMARINES (CI 77007)].

Primary Package

Secondary Package

Outer package